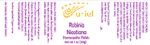 DRUG LABEL: Robinia Nicotiana
NDC: 48951-8374 | Form: PELLET
Manufacturer: Uriel Pharmacy Inc.
Category: homeopathic | Type: HUMAN OTC DRUG LABEL
Date: 20210527

ACTIVE INGREDIENTS: ROBINIA PSEUDOACACIA BARK 4 [hp_X]/1 1; SILVER 6 [hp_X]/1 1; SUS SCROFA ADRENAL GLAND 8 [hp_X]/1 1; TOBACCO LEAF 6 [hp_X]/1 1; STRYCHNOS NUX-VOMICA SEED 6 [hp_X]/1 1; COPPER 8 [hp_X]/1 1; SODIUM PHOSPHATE 10 [hp_X]/1 1
INACTIVE INGREDIENTS: SUCROSE

Robinia Nicotiana

INDICATIONS AND USAGE

Directions: FOR ORAL USE ONLY.

DOSAGE AND ADMINISTRATION

Dissolve pellets under the tongue 3-4 times daily. Ages 12 and older: 10 pellets. Ages 2-11: 5 pellets. Under age 2: Consult a doctor.

ACTIVE INGREDIENT

Active Ingredients: Robinia 4X, Argentum nitricum (Silver nitrate) 6X, Gl. suprarenales sinistra (Bovine left adrenal gland) 8X, Nicotiana (Tobacco) 6X, Nux vomica (Poison nut) 6X, Cuprum met. (Copper) 8X, Natrium phosphoricum (Sodium monohydrogenphosphate) 10X

Inactive Ingredient: Sucrose

PURPOSE

Use: Temporary relief of upset stomach.

KEEP OUT OF REACH OF CHILDREN.

WARNINGS

Warnings: Claims based on traditional homeopathic practice, not accepted medical evidence. Not FDA evaluated. Contains sugar. Diabetics and persons intolerant of sucrose (sugar): Consult a doctor before use. Do not use if allergic to any ingredient. Consult a doctor before use for serious conditions or if conditions worsen or persist. If pregnant or nursing, consult a doctor before use. Do not use if safety seal is broken or missing.

QUESTIONS

Questions? Call 866.642.2858 Uriel, East Troy WI 53120 www.urielpharmacy.com